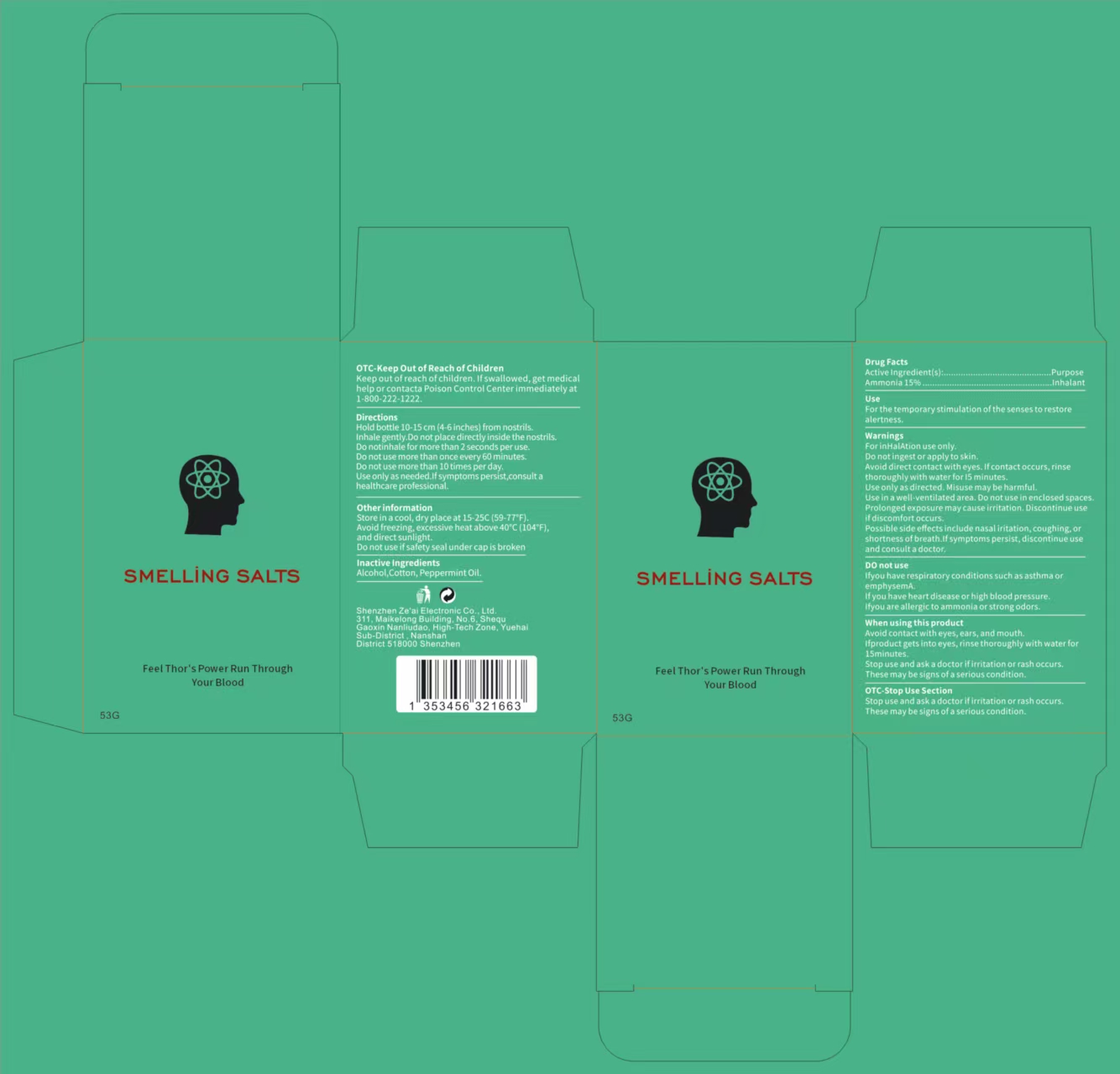 DRUG LABEL: smelling salts
NDC: 85765-002 | Form: POWDER
Manufacturer: Shenzhen Ze'ai Electronic Co., Ltd.
Category: otc | Type: HUMAN OTC DRUG LABEL
Date: 20250910

ACTIVE INGREDIENTS: AMMONIA 15 g/100 g
INACTIVE INGREDIENTS: PEPPERMINT OIL; COTTON; ALCOHOL

85765-002 smelling salts

ACTIVE INGREDIENT

Ammonia 15%

PURPOSE

Inhalant

INDICATIONS AND USAGE

For the temporarystimulation ofthe senses to restore alertness.

WARNINGS

For inHalAtion use only.
Avoid direct contact with eyes.lfcontact occurs,rinse thoroughly with water fori5 minutes.Use only as directed. Misuse may be harmful.
Use in a well-ventilated area.Do notuse in enclosedspaces
Prolonged exposure maycause irritation.Discantinue useifdiscomfort occurs.
Possible side effectsinclude nasallritation,coughing.or shortness of breath.lfsymptoms persist, discontinue use and consulta doctor

Do not ingest or apply to skin.

WHEN USING

Avoid contact with eyes,ears, and mouth.

Ifproduct gets into eyes, rinse thoroughly with water for 15minutes.
Stop use and ask a doctorifirritation orrash occurs.
These may be signs ofaserious condition.

Stop use and ask a doctorifirritation or rash occurs.
These may be signs ofa serious condition.

Keep outofreach ofchildren.lfswallowed,get medical
help or contacta Poison control center immediately at 1-800-222-1222.

INACTIVE INGREDIENT

Alcohol
Cotton
Peppermint Oil